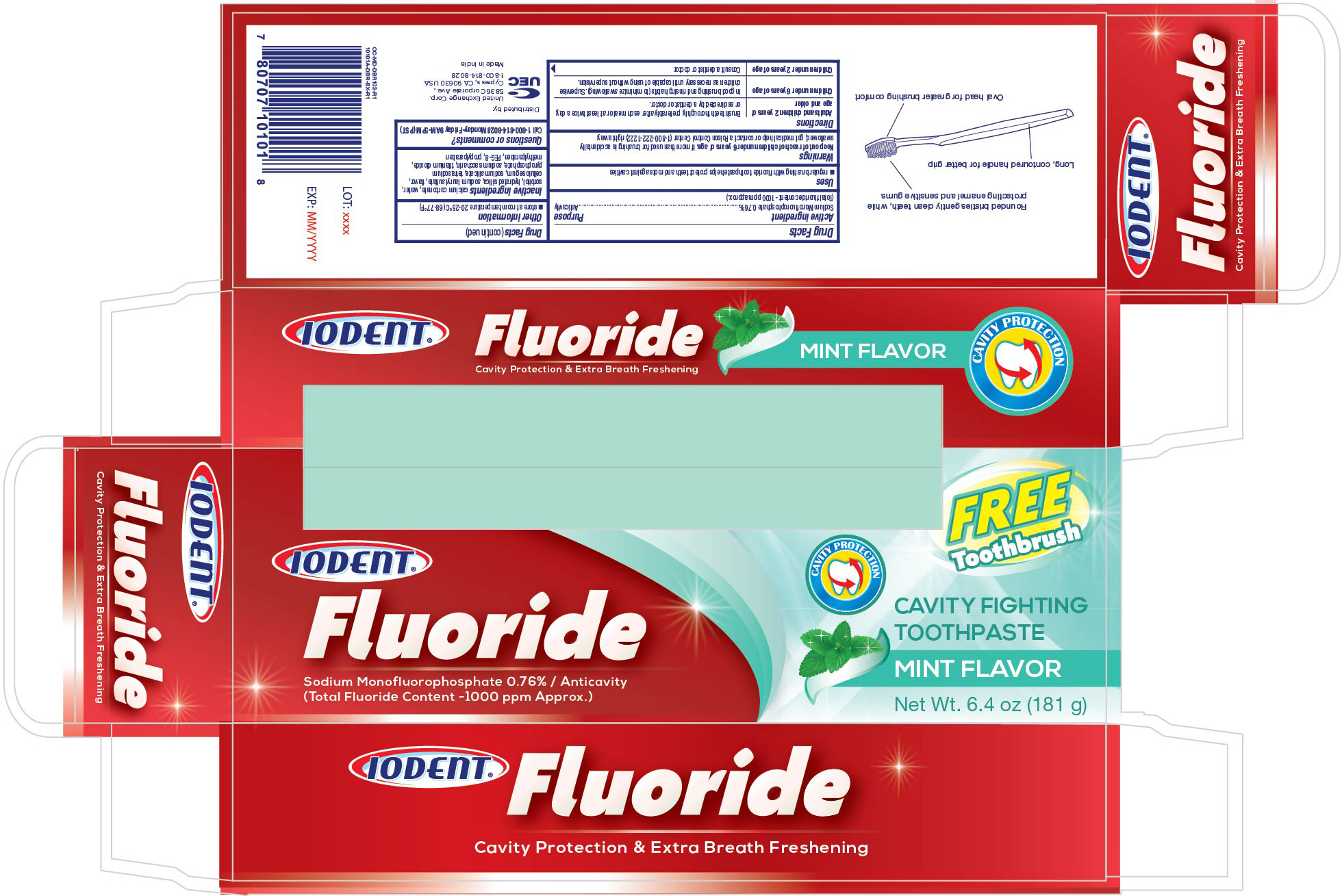 DRUG LABEL: Idodent Flouride Mint
NDC: 65923-181 | Form: PASTE
Manufacturer: United Exchange Corp.
Category: otc | Type: HUMAN OTC DRUG LABEL
Date: 20211124

ACTIVE INGREDIENTS: SODIUM MONOFLUOROPHOSPHATE 0.76 g/100 g
INACTIVE INGREDIENTS: PROPYLPARABEN; METHYLPARABEN; POLYETHYLENE GLYCOL 400; SODIUM LAURYL SULFATE; CALCIUM CARBONATE; WATER; CARBOXYMETHYLCELLULOSE SODIUM, UNSPECIFIED FORM; SORBITOL; HYDRATED SILICA; SACCHARIN SODIUM; SODIUM PYROPHOSPHATE; TITANIUM DIOXIDE; SODIUM SILICATE

Active Ingredient Purpose

Sodium monofluorophosphate 0.76%---------------------------------------------------- Anticavity

(Total Fluoride Content - 1000 ppm Approx.)

Uses

Regular brushing with fluoride toothpaste helps protect teeth and roots against cavities

Warnings

Warnings

Keep out of reach of children under 6 years of age.

In case of accidental overdose, seek professional assistance or contact a Poison Control Center immediately.

Directions

Adults and children 2 years and older | Brush Teeth thoroughly after meals, twice a day, or use as directed by a dentist or physician.
Children under 6 years | To minimize swallowing use a pea-sized amount and supervise brushing until good habits are established.
Children under 2 years | Ask a dentist or physician.

Other Information

Store at room temperature 20-25°C (68-77°F)

Inactive ingredients

calcium carbonate, water, sorbitol, hydrated silica, sodium lauryl sulfate, flavor, cellulose gum, sodium silicate, tetrasodium, propphosphate, sodium saccharin, titanium dioxide, methylparaben, PEG-8, propylparaben

DOSAGE AND ADMINISTRATION

Distributed by:

United Exchange Corp.

17211 Valley View Ave.

Cerritos, CA 90703 USA